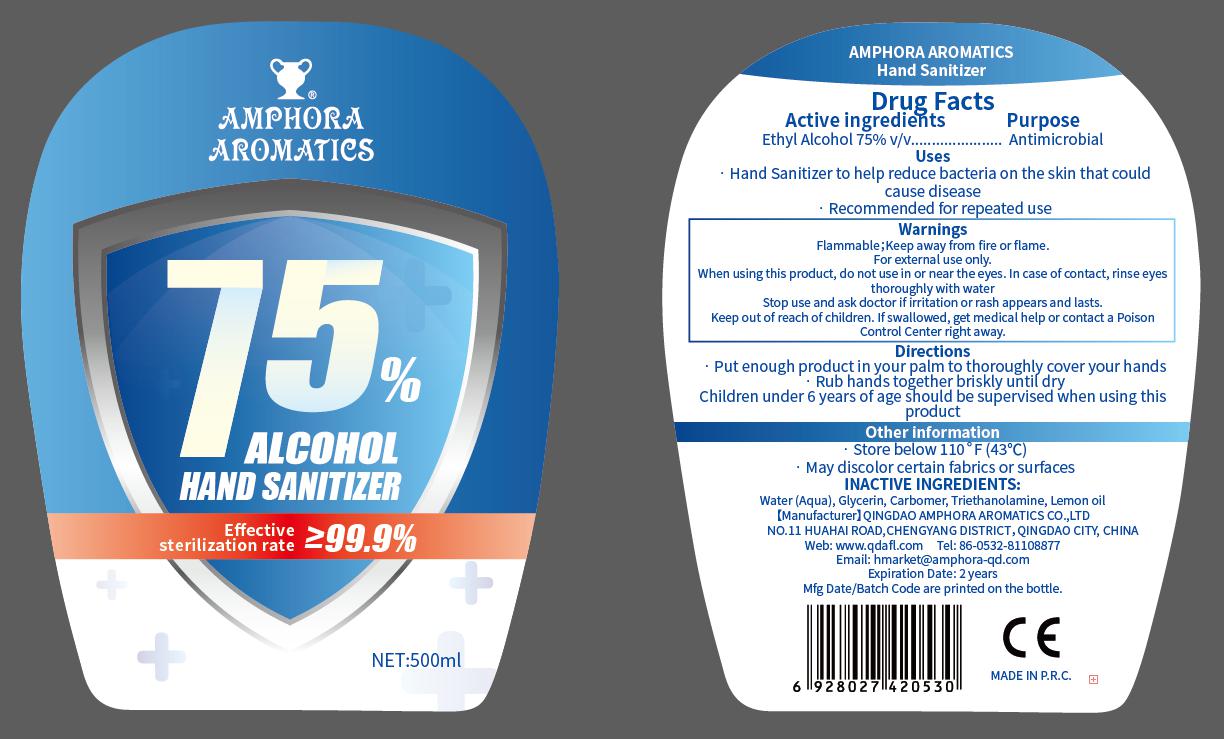 DRUG LABEL: Amphora Aromatics Hand Sanitizer
NDC: 75235-001 | Form: GEL
Manufacturer: QINGDAO AMPHORA AROMATICS CO.,LTD
Category: otc | Type: HUMAN OTC DRUG LABEL
Date: 20200914

ACTIVE INGREDIENTS: ALCOHOL 75 mL/100 mL
INACTIVE INGREDIENTS: TRIETHANOLAMINE LAURYL SULFATE; GLYCERIN; WATER; LEMON OIL; CARBOMER 940

75235-001
Amphora Aromatics Hand Sanitizer

Active Ingredient(s)

Ethyl Alcohol 75% v/v

Purpose

Antimicrobial

Use

· Hand Sanitizer to help reduce bacteria on the skin that could cause disease
· Recommended for re eated use

Warnings

Flammable;Keep away from fire or flame.
For external use only.

When using this product, do not use in or near the eyes. In case of contact, rinse eyes thoroughly with water

Stop use and ask doctor if irritation or rash appears and lasts.

Keep out of reach of children. If swallowed, get medical help or contact a Poison Control Center right away.

do not use in or near the eyes. In case of contact, rinse eyes thoroughly with water

When using this product, do not use in or near the eyes. In case of contact, rinse eyes thoroughly with water

Stop use and ask doctor if irritation or rash appears and lasts.

Keep out of reach of children. If swallowed, get medical help or contact a Poison Control Center right away.

Stop use and ask doctor if irritation or rash appears and lasts.

Keep out of reach of children. If swallowed, get medical help or contact a Poison Control Center right away.

Directions

· Put enough product in your palm to thoroughly cover your hands
· Rub hands together briskly until dry
Children under 6 years of age snould be supervised when using this product

Other information

Store below 110F (43C)
May discolor certain fabrics or surfaces

Inactive ingredients

water(Aqua),carbomer,glycerin,lemon oil,triethanolamine.